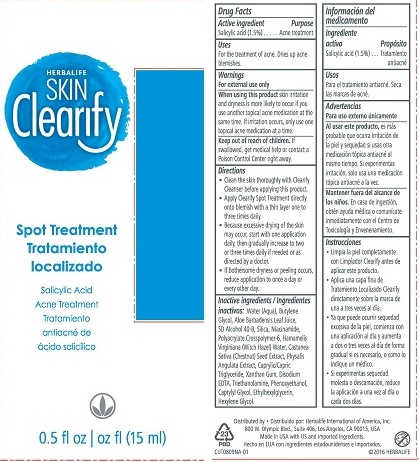 DRUG LABEL: Skin Clearify Spot Treatment
NDC: 51785-809 | Form: LIQUID
Manufacturer: Herbalife International of America Inc.
Category: otc | Type: HUMAN OTC DRUG LABEL
Date: 20161010

ACTIVE INGREDIENTS: SALICYLIC ACID 1.5 mg/100 mL
INACTIVE INGREDIENTS: MEDIUM-CHAIN TRIGLYCERIDES; SILICON DIOXIDE; NIACINAMIDE; PHENOXYETHANOL; WATER; BUTYLENE GLYCOL; ALCOHOL; PHYSALIS ANGULATA; ALOE VERA LEAF; HAMAMELIS VIRGINIANA LEAF WATER; CASTANEA SATIVA WHOLE; ETHYLHEXYLGLYCERIN; XANTHAN GUM; EDETATE DISODIUM; TROLAMINE; CAPRYLYL GLYCOL; HEXYLENE GLYCOL

Clearify Acne Spot Treatment

Drug Facts

Active ingredient

Salicylic acid (1.5%)

Purpose

Acne treatment

Uses

For the treatment of acne. Dries up acne blemishes.

Warnings

For external use only

When using this product skin irritation and dryness is more likely to occur if you use another topical acne medication at the same time. If irritation occurs, only use one topical acne medication at a time.

Keep out of reach of children. If swallowed, get medical help or contact a Poison Control Center right away.

Directions

- Clean the skin thoroughly with Clearify Cleanser before applying this product.
- Apply Clearify Spot Treatment directly onto blemish with a thin layer one to three times daily.
- Because excessive drying of the skin may occur, start with one application daily, then gradually increase to two or three times daily if needed or as directed by a doctor.
- If bothersome dryness or peeling occurs, reduce application to once a day or every other day.

INACTIVE INGREDIENT

Inactive ingredients: Water (Aqua), Butylene Glycol, Aloe Barbadensis Leaf Juice, SD Alcohol 40-B, Silica, Niacinamide, Polyacrylate Crosspolymer-6, Hamamelis Virginiana (Witch Hazel) Water, Castanea Sativa (Chestnut) Seed Extract, Physalis Angulata Extract, Caprylic/Capric Triglyceride, Xanthan Gum, Disodium EDTA, Triethanolamine, Phenoxyethanol, Caprylyl Glycol, Ethylhexylglycerin, Hexylene Glycol.

Distributed by: Herbalife International of America, Inc.

800 W. Olympic Blvd., Suite 406, Los Angeles, CA 90015 USA

Made in USA with US and imported ingredients.

© 2016 HERBALIFE

PACKAGE LABEL

HERBALIFE

SKIN Clearify

Spot Treatment

Salicylic Acid Acne Treatment

0.5 fl oz (15 mL)